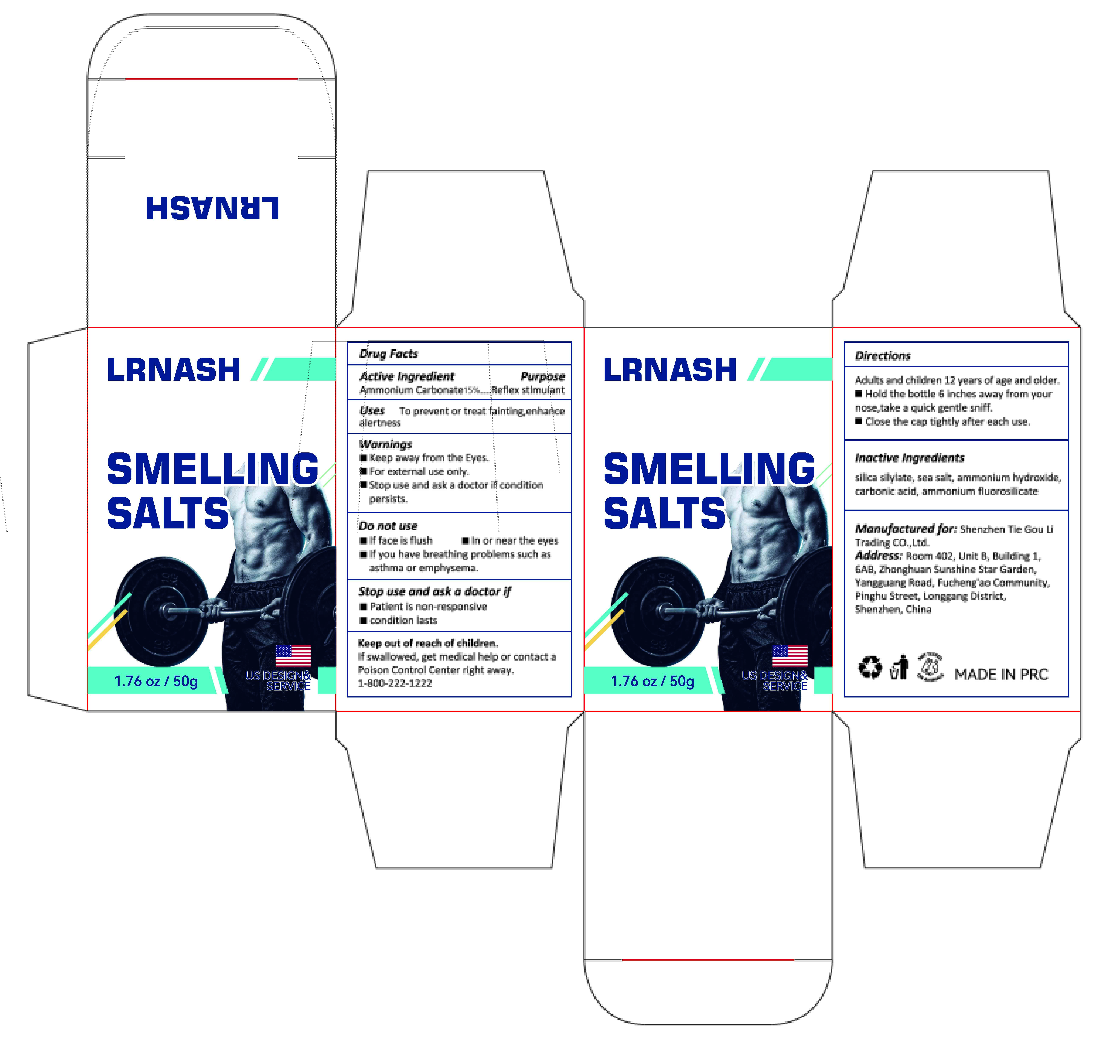 DRUG LABEL: LRNASH SMELLING SALTS
NDC: 85405-001 | Form: GRANULE
Manufacturer: Shenzhen Tie Gou Li Trading Co., Ltd.
Category: otc | Type: HUMAN OTC DRUG LABEL
Date: 20250529

ACTIVE INGREDIENTS: AMMONIUM CARBONATE 15 g/100 g
INACTIVE INGREDIENTS: AMMONIUM HEXAFLUOROSILICATE; SEA SALT; AMMONIA; CARBON DIOXIDE; SILANAMINE

LRNASH SMELLING SALTS

ACTIVE INGREDIENT

Ammonium Carbonate 15%

PURPOSE

Reflex stlmulant

INDICATIONS AND USAGE

Uses To prevent or treat fainting,enhancealertness

WARNINGS

Keep away from the Eyes.
For external use only.
Stop use and ask a doctor if condition persists.

DO NOT USE

lf face is flush
in or near the eyes
lf you have breathing problems such as asthma or emphysema.

WHEN USING

Keep away from the Eyes,
For external use only.

STOP USE

Patient is non-responsive
condition lasts

KEEP OUT OF REACH OF CHILDREN

If swallowed, get medical help or contact a Poison Control Center right away.1-800-222-1222

DOSAGE AND ADMINISTRATION

Adults and children 12 years of age and older.
Hold the bottle 6 inches away from yournose,take a quick gentle sniff.
Close the cap tightly after each use.

INACTIVE INGREDIENT

Silica Silylate
Sea Salt
Ammonium Hydroxide
Carbonic Acid
Ammonium Fluorosilicate